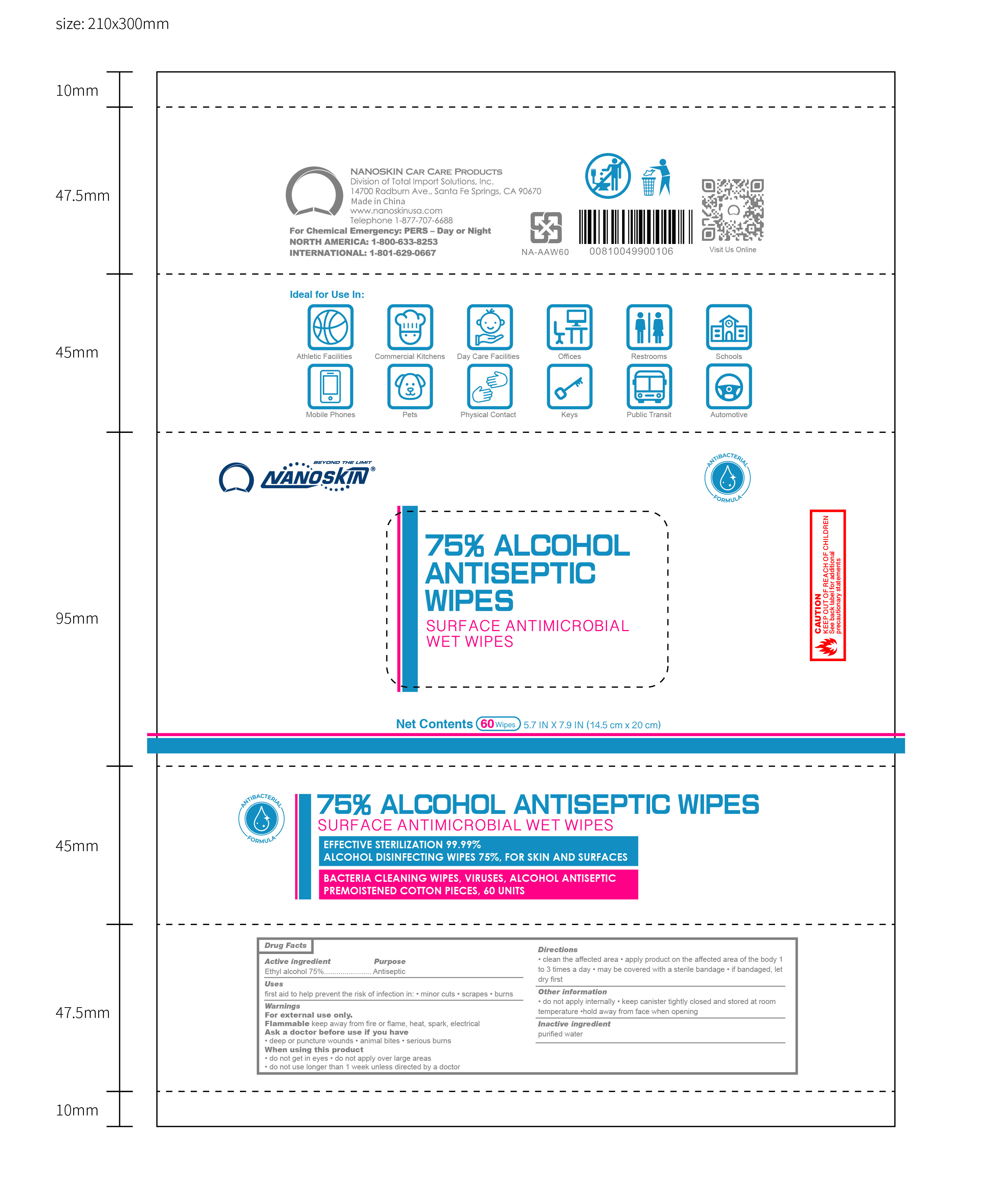 DRUG LABEL: 75% Alcohol Antiseptic Wipe
NDC: 74624-239 | Form: CLOTH
Manufacturer: Total Import Solutions, Inc.
Category: otc | Type: HUMAN OTC DRUG LABEL
Date: 20200511

ACTIVE INGREDIENTS: ALCOHOL 75 mL/100 mL
INACTIVE INGREDIENTS: BENZETHONIUM CHLORIDE 0.001 mL/100 mL; IODOPROPYNYL BUTYLCARBAMATE 0.001 mL/100 mL; WATER 24.998 mL/100 mL

Active Ingredient(s)

Ethanol Alcohol 75% v/v. Purpose: Antiseptic

Use

Antiseptic Wipe to help reduce bacteria that potentially can cause disease. For use when soap and water are not available.

Warnings

For external use only. Flammable. Keep away from heat or flame

Do not use

- in children less than 2 months of age
- on open skin wounds

When using this product keep out of eyes, ears, and mouth. In case of contact with eyes, rinse eyes thoroughly with water.
Stop use and ask a doctor if irritation or rash occurs. These may be signs of a serious condition.
Keep out of reach of children. If swallowed, get medical help or contact a Poison Control Center right away.

Stop use and ask a doctor if irritation or rash occurs. These may be signs of a serious condition.

Keep out of reach of children. If swallowed, get medical help or contact a Poison Control Center right away.

Directions

Antiseptic Wipe to help reduce bacteria that potentially can cause disease. For use when soap and water are not available.

Other information

- Store between 15-30C (59-86F)
- Avoid freezing and excessive heat above 40C (104F)

Inactive ingredients

Water, Benzethonium chloride, IPBC

Package Label - Principal Display Panel

363 mL NDC: 74624-239-60 - Antiseptic Wipes 60 Each